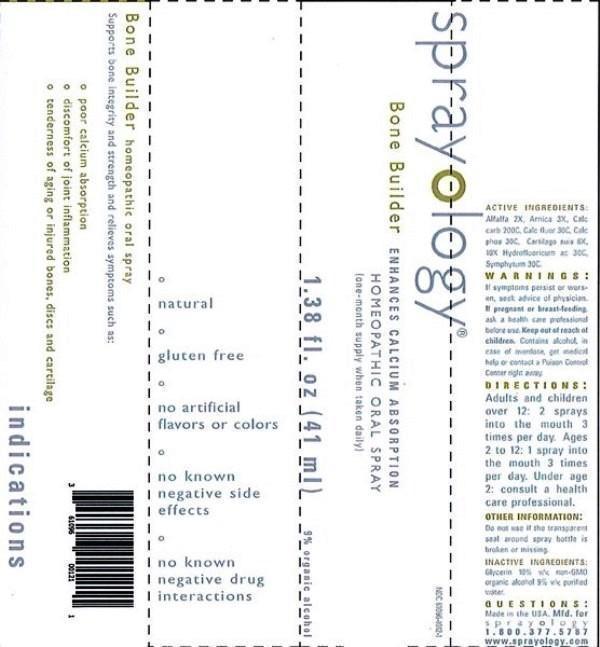 DRUG LABEL: Sprayology Bone Builder
NDC: 61096-1012 | Form: LIQUID
Manufacturer: Eight and Company
Category: homeopathic | Type: HUMAN OTC DRUG LABEL
Date: 20160726

ACTIVE INGREDIENTS: ALFALFA 2 [hp_X]/41 mL; ARNICA MONTANA 3 [hp_X]/41 mL; OYSTER SHELL CALCIUM CARBONATE, CRUDE 200 [hp_C]/41 mL; CALCIUM FLUORIDE 30 [hp_C]/41 mL; TRIBASIC CALCIUM PHOSPHATE 30 [hp_C]/41 mL; SUS SCROFA CARTILAGE 6 [hp_X]/41 mL; HYDROFLUORIC ACID 30 [hp_C]/41 mL; COMFREY ROOT 30 [hp_C]/41 mL
INACTIVE INGREDIENTS: GLYCERIN; ALCOHOL; WATER

Sprayology Bone Builder

ACTIVE INGREDIENT

Active Ingredients: Alfalfa 2X, Arnica montana 3X, Calcarea carbonica 200C, Calcarea fluorica 30C, Calcarea phosphorica 30C, Cartilago suis 6X, 10X, Hydrofluoricum acidum 30C, Symphytum officinale 30C.

WARNINGS

Warnings: If symptoms persist or worsen, seek advice of physician. If pregnant or breast-feeding, ask a health care professional before use. Keep out of reach of children. Contains alcohol, in case of overdose, get medical help or contact a Poison Control Center right away.

Keep out of reach of children.

Directions:

- Adults and children over 12: 2 sprays into the mouth 3 times per day.
- Ages 2 to 12: 1 spray into the mouth 3 times per day.
- Under age 2: consult a health care professional.

PURPOSE

Supports bone integrity and strength and relieves symptoms such as:

- poor calcium absorption
- discomfort of joint inflammation
- tenderness of aging or injured bones, discs and cartilage

Other Information: Do not use if the transparent seal around spray bottle is broken or missing.

INACTIVE INGREDIENT

Inactive Ingredients: Glycerin 10% v/v, non-GMO organic alcohol 9% v/v and purified water.

INDICATIONS AND USAGE

Supports bone integrity and strength and relieves symptoms such as:

° poor calcium absorption

° discomfort of joint inflammation

° tenderness of aging or injured bones, discs and cartilage

° natural

° gluten free

° no artificial flavors or colors

° no known negative side effects

° no known negative drug interactions